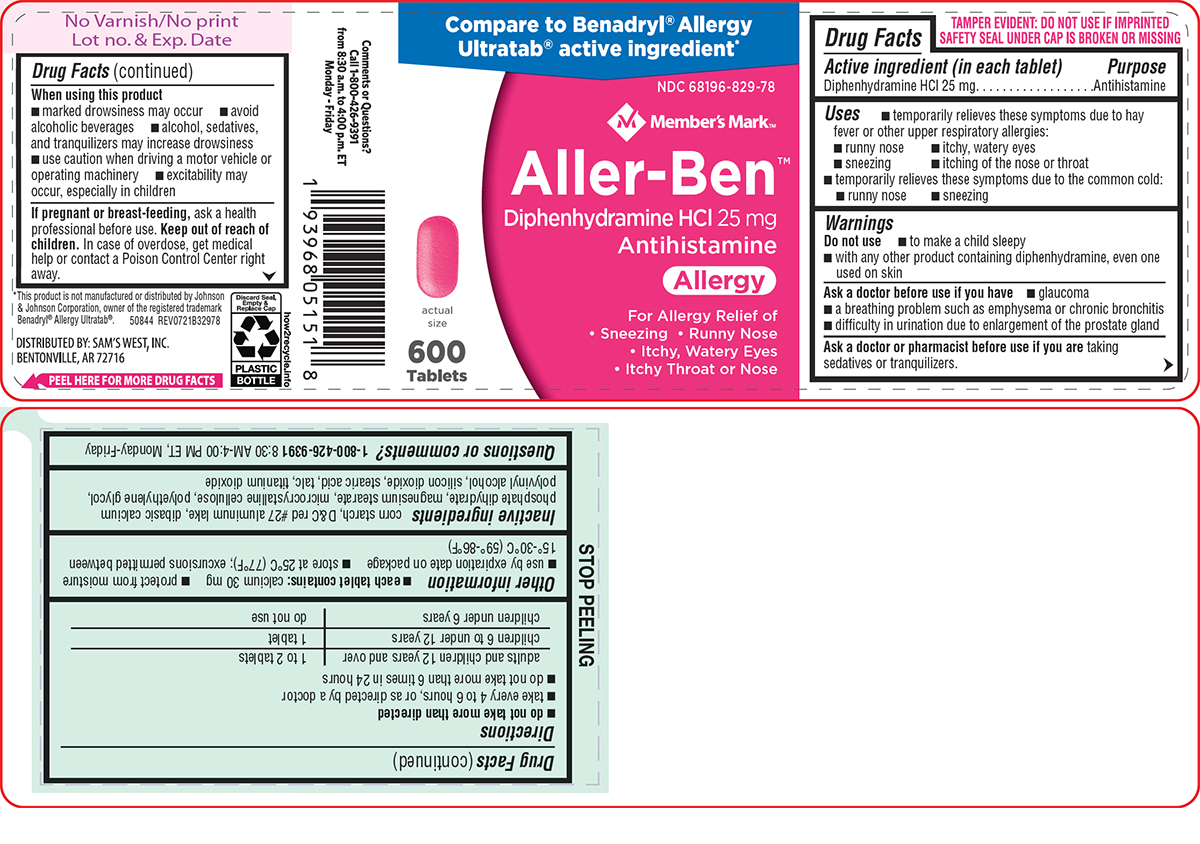 DRUG LABEL: Aller-Ben
NDC: 68196-829 | Form: TABLET, FILM COATED
Manufacturer: Sam's West Inc
Category: otc | Type: HUMAN OTC DRUG LABEL
Date: 20250709

ACTIVE INGREDIENTS: DIPHENHYDRAMINE HYDROCHLORIDE 25 mg/1 1
INACTIVE INGREDIENTS: STARCH, CORN; D&C RED NO. 27 ALUMINUM LAKE; DIBASIC CALCIUM PHOSPHATE DIHYDRATE; MAGNESIUM STEARATE; MICROCRYSTALLINE CELLULOSE; POLYETHYLENE GLYCOL, UNSPECIFIED; POLYVINYL ALCOHOL, UNSPECIFIED; SILICON DIOXIDE; STEARIC ACID; TALC; TITANIUM DIOXIDE

Members Mark 44-329 Aller-Ben

Active ingredient (in each tablet)

Diphenhydramine HCl 25 mg

Purpose

Antihistamine

Uses

- temporarily relieves these symptoms due to hay fever or other upper respiratory allergies:
  - runny nose
  - itchy, watery eyes
  - sneezing
  - itching of the nose or throat
- temporarily relieves these symptoms due to the common cold:
  - runny nose
  - sneezing

Warnings

Do not use

- to make a child sleepy
- with any other product containing diphenhydramine, even one used on skin

Ask a doctor before use if you have

- glaucoma
- a breathing problem such as emphysema or chronic bronchitis
- difficulty in urination due to enlargement of the prostate gland

Ask a doctor or pharmacist before use if you are

taking sedatives or tranquilizers.

When using this product

- marked drowsiness may occur
- avoid alcoholic beverages
- alcohol, sedatives, and tranquilizers may increase drowsiness
- use caution when driving a motor vehicle or operating machinery
- excitability may occur, especially in children

If pregnant or breast-feeding,

ask a health professional before use.

Keep out of reach of children.

In case of overdose, get medical help or contact a Poison Control Center right away.

Directions

- do not take more than directed
- take every 4 to 6 hours, or as directed by a doctor
- do not take more than 6 times in 24 hours

adults and children 12 years and over | 1 to 2 tablets
children 6 to under 12 years | 1 tablet
children under 6 years | do not use

Other information

- each tablet contains: calcium 30 mg
- protect from moisture
- use by expiration date on package
- store at 25°C (77°F); excursions permitted between 15°-30°C (59°-86°F)

Inactive ingredients

corn starch, D&C red #27 aluminum lake, dibasic calcium phosphate dihydrate, magnesium stearate, microcrystalline cellulose, polyethylene glycol, polyvinyl alcohol, silicon dioxide, stearic acid, talc, titanium dioxide

Questions or comments?

1-800-426-9391 8:30 AM-4:00 PM ET, Monday-Friday

Principal display panel

Compare to Benadryl® Allergy
Ultratab® active ingredient*

NDC 68196-829-78

Member's Mark™

Aller-Ben™

Diphenhydramine HCl 25 mg
Antihistamine
Allergy

For Allergy Relief of
• Sneezing • Runny Nose
• Itchy, Watery Eyes
• Itchy Throat or Nose

actual
size

600
Tablets

TAMPER EVIDENT: DO NOT USE IF IMPRINTED
SAFETY SEAL UNDER CAP IS BROKEN OR MISSING

Comments or Questions?
Call 1-800-426-9391
from 8:30a.m. to 4:00p.m. ET
Monday-Friday

*This product is not manufactured or distributed by Johnson
& Johnson Corporation, owner of the registered trademark
Benadryl® Allergy Ultratab®. 50844 REV0721B32978

DISTRIBUTED BY: SAM'S WEST, INC.,
BENTONVILLE, AR 72716

Members Mark 44-329